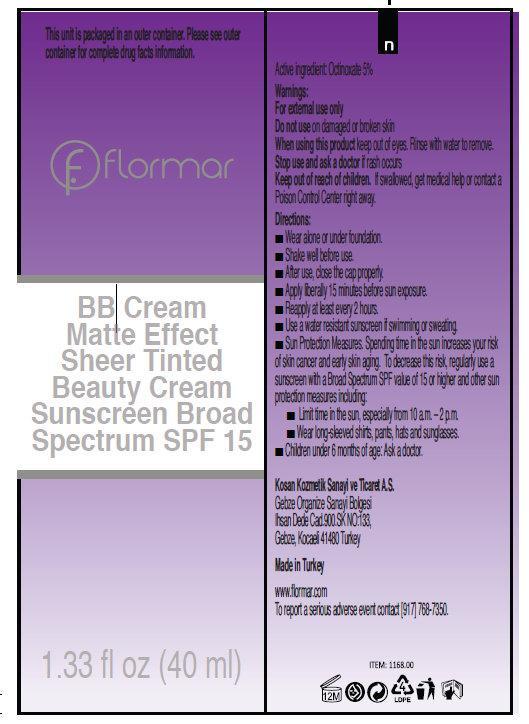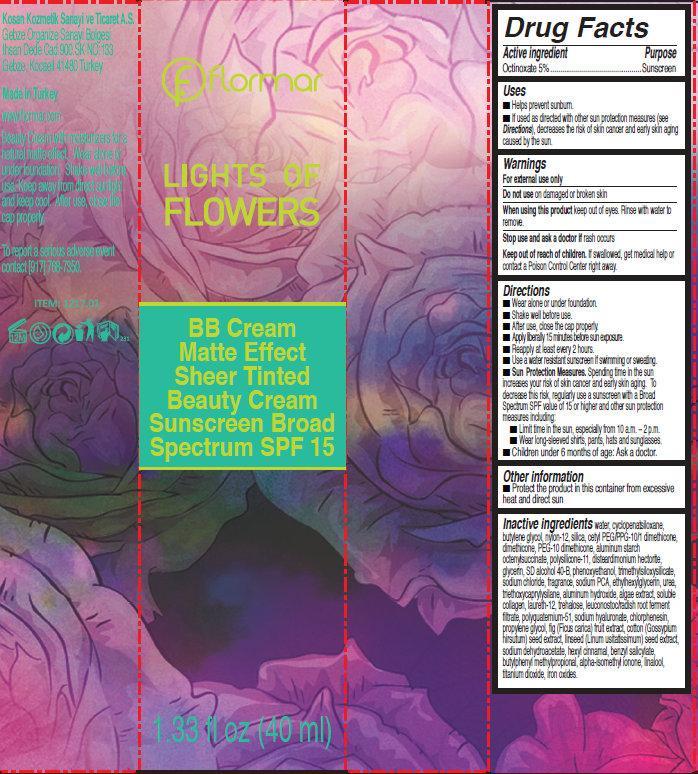 DRUG LABEL: flormar BB Matte Effect Sheer Tinted Beauty Cream Sunscreen Broad Spectrum SPF 15 LF51 Light
NDC: 61722-120 | Form: CREAM
Manufacturer: Kosan Kozmetik Sanayi ve Ticaret A.S.
Category: otc | Type: HUMAN OTC DRUG LABEL
Date: 20191018

ACTIVE INGREDIENTS: OCTINOXATE 50 mg/1 mL
INACTIVE INGREDIENTS: WATER; CYCLOMETHICONE 5; BUTYLENE GLYCOL; NYLON-12; SILICON DIOXIDE; DIMETHICONE; ALUMINUM STARCH OCTENYLSUCCINATE; DISTEARDIMONIUM HECTORITE; GLYCERIN; PHENOXYETHANOL; SODIUM CHLORIDE; SODIUM PYRROLIDONE CARBOXYLATE; ETHYLHEXYLGLYCERIN; TRIETHOXYCAPRYLYLSILANE; ALUMINUM HYDROXIDE; LAURETH-12; TREHALOSE; LEUCONOSTOC/RADISH ROOT FERMENT FILTRATE; HYALURONATE SODIUM; SODIUM DEHYDROACETATE; .ALPHA.-HEXYLCINNAMALDEHYDE; BENZYL SALICYLATE; BUTYLPHENYL METHYLPROPIONAL; ISOMETHYL-.ALPHA.-IONONE; LINALOOL, (+/-)-; TITANIUM DIOXIDE; FERRIC OXIDE RED

flormar BB Cream Matte Effect Sheer Tinted Beauty Cream Sunscreen Broad Spectrum SPF 15 LF51 Light

Active Ingredient

Octinoxate 5%

Purpose

Sunscreen

Uses

- Helps prevent sunburn.
- If used as directed with other sun protection measures (see Directions), decreases the risk of skin cancer and early skin aging caused by the sun.

Warnings

For external use only

Do not use

on damaged or broken skin

When using this product

keep out of eyes. Rinse with water to remove.

Stop use and ask a doctor if

rash occurs

Keep out of reach of children.

If swallowed, get medical help or contact a Poison Control Center right away.

Directions

- Wear alone or under foundation.
- Shake well before use.
- Apply drop by drop with fingertips.
- Apply liberally 15 minutes before sun exposure.
- Reapply at least every 2 hours.
- Use a water resistant sunscreen if swimming or sweating.
- Sun Protection Measures. Spending time in the sun increases your risk of skin cancer and early skin aging. To decrease this risk, regularly use a sunscreen with a Broad Spectrum SPF value of 15 or higher and other sun protection measures including:
-
  - Limit time in the sun, especially from 10 a.m. – 2 p.m.
  - Wear long-sleeved shirts, pants, hats and sunglasses.
- Children under 6 months of age: Ask a doctor.

Other information

- Protect the product in this container from excessive heat and direct sun

Inactive ingredients

water, cyclopentasiloxane, butylene glycol, nylon 12, silica, cetyl peg/ppg-10/1 dimethicone, dimethicone, peg-10 dimethicone, aluminum starch octenylsuccinate, polysilicone-11, disteardimonium hectorite, glycerin, sd alcohol 40-b, phenoxyethanol, trimethylsiloxysilicate, sodium chloride, fragrance, sodium pca, ethylhexylglycerin, uree, triethoxycaprylylsilane, aluminum hydroxide, algae extract, soluble collagen, laureth-12, trehalose,leuconostoc/radish root ferment filtrate, polyquaternium-51, sodium hyaluronate, chlorphenesin propylene glycol, fig (ficus carica) fruit extract, cotton (gossypium hirsutum) seed extract, linseed (linum usitatissimum) seed extract, sodium dehydroacetate, hexyl cinnamal, benzyl salicylate, butylphenyl methylpropional, alpha-isomethyl ionone, linalool, titanium dioxide, iron oxides